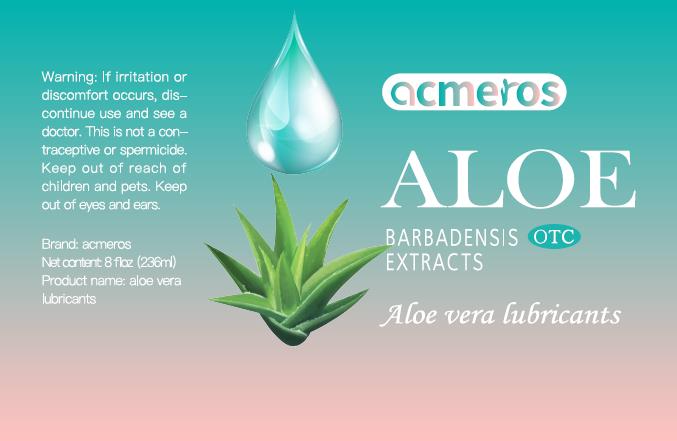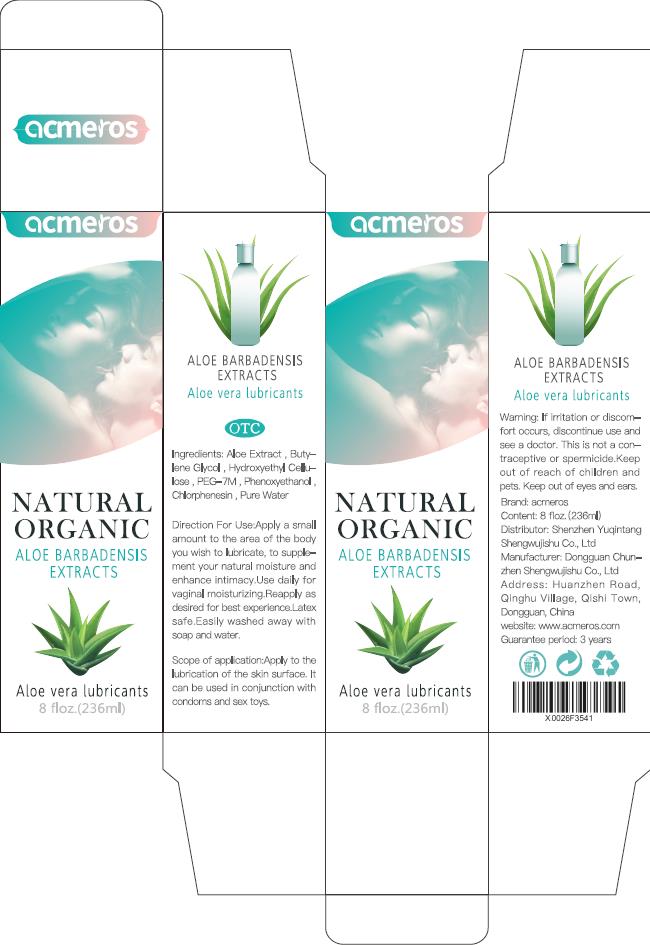 DRUG LABEL: acmeros Lubricant X0026F3541
NDC: 73194-212 | Form: OIL
Manufacturer: Shenzhen Yuqintang Shengwu Jishu Co., Ltd.
Category: otc | Type: HUMAN OTC DRUG LABEL
Date: 20201123

ACTIVE INGREDIENTS: BUTYLENE GLYCOL 47.2 g/236 mL
INACTIVE INGREDIENTS: ALOIN 23.6 mL/236 mL; HYDROXYETHYL CELLULOSE (280 MPA.S AT 2%) 3.776 mL/236 mL; WATER 159.3472 mL/236 mL; PHENOXYETHANOL 0.708 mL/236 mL; POLYETHYLENE GLYCOL 300000 1.18 mL/236 mL; CHLORPHENESIN 0.1888 mL/236 mL

Shenzhen YuQinTang, Lubricant, acmeros, X0026F3541

Active ingredient

butylene glycol (20%): 47.2g(mL)/package

Inactive ingredient

water (67.52%): 159.3472mL/package

aloe extract (10%): 23.6mL/package

hydroxyethylcellulose (1.6%): 3.776mL/package

polyethylene glycol 300000 (0.5%): 1.18mL/package

phenoxyethanol (0.3%): 0.708mL/package

chlorphenesin (0.08%): 0.1888mL/package

Purpose

This lubricant is made from high quality raw materials.

It can achieve higher lubricantion, longer lubrication time and less dosage.

When using

Virginal dryness and/or intimate sexual activity.

Do not use when wound or skin infection.

Stop use

If irritation or discomfort occurs, discontinue use and see a doctor.
Very slippery on surfaces, clean spills immediately.

Ask doctor

If irritation or discomfort occurs, discontinue use and see a doctor.

Ask doctor/pharmacist when you current use other drugs.

Keep out of reach of children and pets.

Questions

Please contact us when you have any questions.

Pregnancy or breast feeding

Pregnant or breast feeding women shall follow doctor advice.

Indications & usage

This product is a water-based personal lubricant, for penile and/or vaginal application, intended to lubricate and moisturize, to enhance the ease and comfort of intimate sexual activity, help relieve virginal dryness, and supplement to the body's natural lubricant.

Apply a small amount to genital areas. Reapply as needed or desired.

Dosage & administration

One bottle of 236mL in one bottle/package.

Apply a small amount to the area of the body you wish to lubricate.

Dosage forms & strengths

The lubricant is like oil form. Strengths: 20%.

A small amount one time, or reapply as needed or desired.

Warnings

If irritation or discomfort occurs, discontinue use and see a doctor.
This is not a contraceptive or spermicide.

Keep out of reach of children and pets.
Keep out of eyes and ears.

Package label. Principal display panel

Container

Package